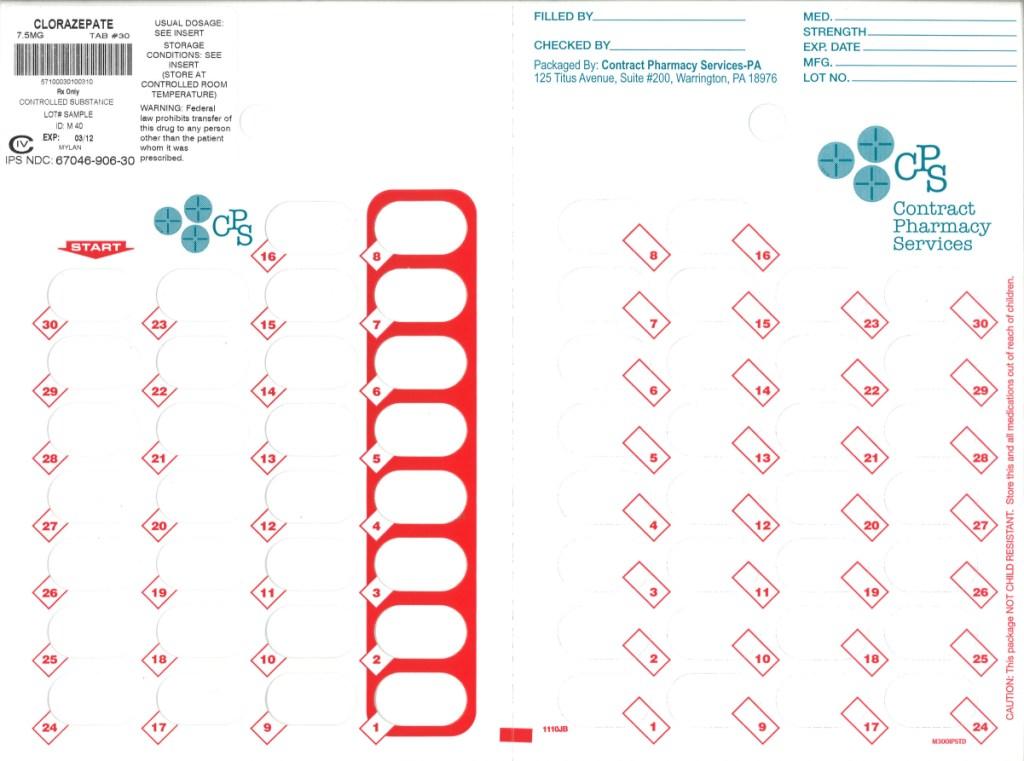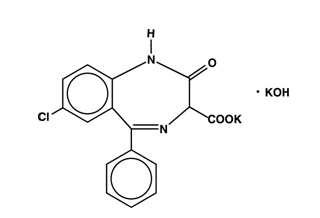 DRUG LABEL: Clorazepate Dipotassium
NDC: 67046-906 | Form: TABLET
Manufacturer: Contract Pharmacy Services-PA
Category: prescription | Type: HUMAN PRESCRIPTION DRUG LABEL
Date: 20101216
DEA Schedule: CIV

ACTIVE INGREDIENTS: CLORAZEPATE DIPOTASSIUM 7.5 mg/1 1
INACTIVE INGREDIENTS: CROSCARMELLOSE SODIUM; FD&C YELLOW NO. 6; MAGNESIUM OXIDE; MAGNESIUM STEARATE; POTASSIUM CARBONATE; SODIUM CHLORIDE; SODIUM LAURYL SULFATE

Clorazepate
Dipotassium Tablets USP, 7.5 mg

CIV

Rx only

DESCRIPTION

Chemically, clorazepate dipotassium is a benzodiazepine. The empirical formula is C16H11ClK2N2O4; the molecular weight is 408.92; 1H-1, 4-Benzodiazepine-3-carboxylic acid, 7-chloro-2,3-dihydro-2-oxo-5-phenyl-, potassium salt compound with potassium hydroxide (1:1) and the structural formula may be represented as follows:

The compound occurs as a fine, light yellow, practically odorless powder. It is insoluble in the common organic solvents, but very soluble in water. Aqueous solutions are unstable, clear, light yellow, and alkaline

Clorazepate Dipotassium Tablets, USP for oral administration, contain 3.75 mg, 7.5 mg or 15 mg of clorazepate dipotassium, USP. In addition, each tablet contains the following inactive ingredients: croscarmellose sodium, magnesium oxide, magnesium stearate, microcrystalline cellulose, potassium carbonate, sodium chloride, sodium lauryl sulfate and the following coloring agents:

3.75 mg - FD&C Blue No. 2 Aluminum Lake

7.5 mg - FD&C Yellow No. 6 Aluminum Lake

CLINICAL PHARMACOLOGY

Pharmacologically, clorazepate dipotassium has the characteristics of the benzodiazepines. It has depressant effects on the central nervous system. The primary metabolite, nordiazepam, quickly appears in the blood stream. The serum half-life is about 2 days. The drug is metabolized in the liver and excreted primarily in the urine. Studies in healthy men have shown that clorazepate dipotassium has depressant effects on the central nervous system. Prolonged administration of single daily doses as high as 120 mg was without toxic effects. Abrupt cessation of high doses was followed in some patients by nervousness, insomnia, irritability, diarrhea, muscle aches, or memory impairment.

Since orally administered clorazepate dipotassium is rapidly decarboxylated to form nordiazepam, there is essentially no circulating parent drug. Nordiazepam, the primary metabolite, quickly appears in the blood and is eliminated from the plasma with an apparent half-life of about 40 to 50 hours. Plasma levels of nordiazepam increase proportionally with Clorazepate Dipotassium dose and show moderate accumulation with repeated administration. The protein binding of nordiazepam in plasma is high (97-98%).

Within 10 days after oral administration of a 15 mg (50µCi) dose of ^14C-Clorazepate Dipotassium to two volunteers, 62-67% of the radioactivity was excreted in the urine and 15-19% was eliminated in the feces. Both subjects were still excreting measurable amounts of radioactivity in the urine (about l% of the ^14C-dose) on day ten.

Nordiazepam is further metabolized by hydroxylation. The major urinary metabolite is conjugated oxazepam (3-hydroxynordiazepam), and smaller amounts of conjugated p-hydroxynordiazepam and nordiazepam are also found in the urine.

INDICATIONS AND USAGE

Clorazepate dipotassium is indicated for the management of anxiety disorders or for the short-term relief of the symptoms of anxiety. Anxiety or tension associated with the stress of everyday life usually does not require treatment with an anxiolytic.

Clorazepate dipotassium tablets are indicated as adjunctive therapy in the management of partial seizures.

The effectiveness of clorazepate dipotassium tablets in long-term management of anxiety, that is, more than 4 months, has not been assessed by systematic clinical studies. Long-term studies in epileptic patients, however, have shown continued therapeutic activity. The physician should reassess periodically the usefulness of the drug for the individual patient.

Clorazepate dipotassium tablets are indicated for the symptomatic relief of acute alcohol withdrawal.

CONTRAINDICATIONS

Clorazepate dipotassium tablets are contraindicated in patients with a known hypersensitivity to the drug and in those with acute narrow angle glaucoma.

WARNINGS

Clorazepate dipotassium tablets are not recommended for use in depressive neuroses or in psychotic reactions.

Patients taking clorazepate dipotassium tablets should be cautioned against engaging in hazardous occupations requiring mental alertness, such as operating dangerous machinery including motor vehicles.

Since clorazepate dipotassium has a central nervous system depressant effect, patients should be advised against the simultaneous use of other CNS-depressant drugs, and cautioned that the effects of alcohol may be increased.

Because of the lack of sufficient clinical experience, clorazepate dipotassium tablets are not recommended for use in patients less than 9 years of age.

Physical and Psychological Dependence

Withdrawal symptoms (similar in character to those noted with barbiturates and alcohol) have occurred following abrupt discontinuance of clorazepate. Withdrawal symptoms associated with the abrupt discontinuation of benzodiazepines have included convulsions, delirium, tremor, abdominal and muscle cramps, vomiting, sweating, nervousness, insomnia, irritability, diarrhea, and memory impairment. The more severe withdrawal symptoms have usually been limited to those patients who had received excessive doses over an extended period of time. Generally milder withdrawal symptoms have been reported following abrupt discontinuance of benzodiazepines taken continuously at therapeutic levels for several months. Consequently, after extended therapy, abrupt discontinuation of clorazepate should generally be avoided and a gradual dosage tapering schedule followed.

Caution should be observed in patients who are considered to have a psychological potential for drug dependence.

Evidence of drug dependence has been observed in dogs and rabbits which was characterized by convulsive seizures when the drug was abruptly withdrawn or the dose was reduced; the syndrome in dogs could be abolished by administration of clorazepate.

Usage in Pregnancy

An increased risk of congenital malformations associated with the use of minor tranquilizers (chlordiazepoxide, diazepam, and meprobamate) during the first trimester of pregnancy has been suggested in several studies. Clorazepate dipotassium, a benzodiazepine derivative, has not been studied adequately to determine whether it, too, may be associated with an increased risk of fetal abnormality. Because use of these drugs is rarely a matter of urgency, their use during this period should almost always be avoided. The possibility that a woman of childbearing potential may be pregnant at the time of institution of therapy should be considered. Patients should be advised that if they become pregnant during therapy or intend to become pregnant they should communicate with their physician about the desirability of discontinuing the drug.

Usage during Lactation

Clorazepate dipotassium tablets should not be given to nursing mothers since it has been reported that nordiazepam is excreted in human breast milk.

PRECAUTIONS

In those patients in which a degree of depression accompanies the anxiety, suicidal tendencies may be present and protective measures may be required. The least amount of drug that is feasible should be available to the patient.

Patients taking clorazepate dipotassium tablets for prolonged periods should have blood counts and liver function tests periodically. The usual precautions in treating patients with impaired renal or hepatic function should also be observed.

In elderly or debilitated patients, the initial dose should be small, and increments should be made gradually, in accordance with the response of the patient to preclude ataxia or excessive sedation.

Information for Patients

To assure the safe and effective use of benzodiazepines, patients should be informed that, since benzodiazepines may produce psychological and physical dependence, it is essential that they consult with their physician before either increasing the dose or abruptly discontinuing this drug.

Pediatric Use

See WARNINGS.

Geriatric Use

Clinical studies of clorazepate dipotassium studies were not adequate to determine whether subjects aged 65 and over respond differently than younger subjects. Elderly or debilitated patients may be especially sensitive to the effects of all benzodiazepines, including clorazepate dipotassium. In general, elderly or debilitated patients should be started on lower doses of clorazepate dipotassium tablets and observed closely, reflecting the greater frequency of decreased hepatic, renal, or cardiac function, and concomitant disease or other drug therapy. Dose adjustments should also be made slowly, and with more caution in this patient population (see PRECAUTIONS and DOSAGE AND ADMINISTRATION).

ADVERSE REACTIONS

The side effect most frequently reported was drowsiness. Less commonly reported (in descending order of occurrence) were: dizziness, various gastrointestinal complaints, nervousness, blurred vision, dry mouth, headache, and mental confusion. Other side effects included insomnia, transient skin rashes, fatigue, ataxia, genitourinary complaints, irritability, diplopia, depression, tremor and slurred speech.

There have been reports of abnormal liver and kidney function tests and of decrease in hematocrit.

Decrease in systolic blood pressure has been observed.

DOSAGE AND ADMINISTRATION

For the symptomatic relief of anxiety

Clorazepate dipotassium tablets are administered orally in divided doses. The usual daily dose is 30 mg. The dose should be adjusted gradually within the range of 15 to 60 mg daily in accordance with the response of the patient. In elderly or debilitated patients it is advisable to initiate treatment at a daily dose of 7.5 to 15 mg.

Clorazepate dipotassium tablets may also be administered in a single dose daily at bedtime; the recommended initial dose is 15 mg. After the initial dose, the response of the patient may require adjustment of subsequent dosage. Lower doses may be indicated in the elderly patient. Drowsiness may occur at the initiation of treatment and with dosage increment.

For the symptomatic relief of acute alcohol withdrawal

The following dosage schedule is recommended

1st 24 hours (Day 1) | 30 mg initially, followed by 30 to 60 mg in divided doses
2nd 24 hours (Day 2) | 45 to 90 mg in divided doses
3rd 24 hours (Day 3) | 22.5 to 45 mg in divided doses
Day 4 | 15 to 30 mg in divided doses

Thereafter, gradually reduce the daily dose to 7.5 to 15 mg. Discontinue drug therapy as soon as patient's condition is stable.

The maximum recommended total daily dose is 90 mg. Avoid excessive reductions in the total amount of drug administered on successive days.

As an Adjunct to Antiepileptic Drugs

In order to minimize drowsiness, the recommended initial dosages and dosage increments should not be exceeded.

Adults

The maximum recommended initial dose in patients over 12 years old is 7.5 mg three times a day. Dosage should be increased by no more than 7.5 mg every week and should not exceed 90 mg/day.

Children (9-12 years)

The maximum recommended initial dose is 7.5 mg two times a day. Dosage should be increased by no more than 7.5 mg every week and should not exceed 60 mg/day.

DRUG INTERACTIONS

If clorazepate dipotassium is to be combined with other drugs acting on the central nervous system, careful consideration should be given to the pharmacology of the agents to be employed. Animal experience indicates that clorazepate dipotassium prolongs the sleeping time after hexobarbital or after ethyl alcohol, increases the inhibitory effects of chlorpromazine, but does not exhibit monoamine oxidase inhibition. Clinical studies have shown increased sedation with concurrent hypnotic medications. The actions of the benzodiazepines may be potentiated by barbiturates, narcotics, phenothiazines, monoamine oxidase inhibitors or other antidepressants.

If clorazepate dipotassium tablets are used to treat anxiety associated with somatic disease states, careful attention must be paid to possible drug interaction with concomitant medication.

In bioavailability studies with normal subjects, the concurrent administration of antacids at therapeutic levels did not significantly influence the bioavailability of clorazepate dipotassium tablets.

OVERDOSAGE

Overdosage is usually manifested by varying degrees of CNS depression ranging from slight sedation to coma. As in the management of overdosage with any drug, it should be borne in mind that multiple agents may have been taken.

The treatment of overdosage should consist of the general measures employed in the management of overdosage of any CNS depressant. Gastric evacuation either by the induction of emesis, lavage, or both, should be performed immediately. General supportive care, including frequent monitoring of the vital signs and close observation of the patient is indicated. Hypotension though rarely reported, may occur with large overdoses. In such cases the use of agents such as Levophed® Bitartrate (norepinephrine bitartrate injection, USP) or Aramine® Injection metaraminol bitartrate injection, USP) should be considered.

While reports indicate that individuals have survived overdoses of clorazepate dipotassium as high as 450 to 675 mg, these doses are not necessarily an accurate indication of the amount of drug absorbed since the time interval between ingestion and the institution of treatment was not always known. Sedation in varying degrees was the most common physiological manifestation of clorazepate dipotassium overdosage. Deep coma when it occurred was usually associated with the ingestion of other drugs in addition to clorazepate dipotassium.

Flumazenil, a specific benzodiazepine receptor antagonist, is indicated for the complete or partial reversal of the sedative effects of benzodiazepines and may be used in situations when an overdose with a benzodiazepine is known or suspected. Prior to the administration of flumazenil, necessary measures should be instituted to secure airway, ventilation, and intravenous access. Flumazenil is intended as an adjunct to, not as a substitute for, proper management of benzodiazepine overdose. Patients treated with flumazenil should be monitored for resedation, respiratory depression, and other residual benzodiazepine effects for an appropriate period after treatment. The prescriber should be aware of a risk of seizure in association with flumazenil treatment, particularly in long-term benzodiazepine users and in cyclic antidepressant overdose. The complete flumazenil package insert including CONTRAINDICATIONS, WARNINGS, and PRECAUTIONS should be consulted prior to use

ANIMAL PHARMACOLOGY AND TOXICOLOGY

Studies in rats and monkeys have shown a substantial difference between doses producing tranquilizing, sedative and toxic effects. In rats, conditioned avoidance response was inhibited at an oral dose of 10 mg/kg; sedation was induced at 32 mg/kg; the LD50 was 1320 mg/kg. In monkeys aggressive behavior was reduced at an oral dose of 0.25 mg/kg; sedation (ataxia) was induced at 7.5 mg/kg; the LD50 could not be determined because of the emetic effect of large doses, but the LD50 exceeds 1600 mg/kg.

Twenty-four dogs were given clorazepate dipotassium orally in a 22-month toxicity study; doses up to 75 mg/kg were given. Drug-related changes occurred in the liver; weight was increased and cholestasis with minimal hepatocellular damage was found, but lobular architecture remained well preserved.

Eighteen rhesus monkeys were given oral doses of clorazepate dipotassium from 3 to 36 mg/kg daily for 52 weeks. All treated animals remained similar to control animals. Although total leucocyte count remained within normal limits it tended to fall in the female animals on the highest doses.

Examination of all organs revealed no alterations attributable to clorazepate dipotassium. There was no damage to liver function or structure.

Reproduction Studies

Standard fertility, reproduction, and teratology studies were conducted in rats and rabbits. Oral doses in rats up to 150 mg/kg and in rabbits up to 15 mg/kg produced no abnormalities in the fetuses. Clorazepate dipotassium did not alter the fertility indices or reproductive capacity of adult animals. As expected, the sedative effect of high doses interfered with care of the young by their mothers (see Usage in Pregnancy).

HOW SUPPLIED

The 7.5 mg tablets are peach round, scored tablets debossed with M above the score and 40 below the score on one side of the tablet and blank on the other side. They are available as follows:

NDC 67046-906-30
blister of 30 tablets

Recommended storage

Protect from moisture. Keep bottle tightly closed. Store between 20° to 25°C (68° to 70°F) [see USP Controlled Room temperature]. Dispense in a USP tight, light-resistant container.

Mylan Pharmaceuticals Inc.
Morgantown, WV 26505

Repackaged by:
Contract Pharmacy Services-PA
125 Titus Ave Suite 200
Warrington, PA 18976 USA

Original--3/2011--NJW

Principal Display Panel

7.5 mg Tablets